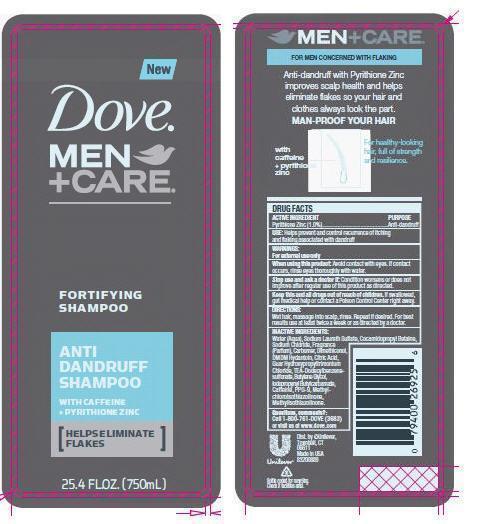 DRUG LABEL: DOVE
NDC: 64942-1273 | Form: SHAMPOO
Manufacturer: Conopco Inc. d/b/a Unilever
Category: otc | Type: HUMAN OTC DRUG LABEL
Date: 20130822

ACTIVE INGREDIENTS: Pyrithione Zinc 1.0 g/100 mL
INACTIVE INGREDIENTS: WATER; SODIUM LAURETH SULFATE; COCAMIDOPROPYL BETAINE; SODIUM CHLORIDE; DMDM HYDANTOIN; TRIETHANOLAMINE DODECYLBENZENESULFONATE; CITRIC ACID MONOHYDRATE; PPG-9; METHYLCHLOROISOTHIAZOLINONE; METHYLISOTHIAZOLINONE; GUAR HYDROXYPROPYLTRIMONIUM CHLORIDE (1.7 SUBSTITUENTS PER SACCHARIDE); DIMETHICONOL (41 MPA.S); CAFFEINE

Dove Men plus Care Anti Dandruff Shampoo

ACTIVE INGREDIENT

Pyrithione Zinc (1.0%)

PURPOSE

Antidandruff

INDICATIONS AND USAGE

USE: helps prevent and control recurrence of itching and flaking associated with dandruff

WARNINGS:
For external use only

When using this product: Avoid contact with eyes. If contact occurs, rinse eyes thoroughly with water.

Stop use and ask a doctor if: Condition worsens or does not improve after regular use of this product as directed.

KEEP OUT OF REACH OF CHILDREN

Keep this and all drugs out of reach of children. If swallowed, get medical help or contact a Poison Control Center right away.

DOSAGE AND ADMINISTRATION

DIRECTIONS: Wet hair, massage into scalp, rinse. Repeat if desired. For best results use at least twice a week or as directed by a doctor.

INACTIVE INGREDIENT

INACTIVE INGREDIENTS:Water (Aqua), Sodium Laureth Sulfate, Cocamidopropyl Betaine, Sodium Chloride, Fragrance (Parfum), Carbomer, Dimethiconol, DMDM Hydantoin, Citric Acid, Guar Hydroxypropyltrimonium Chloride, TEA-Dodecylbenzenesulfonate, Butylene Glycol, Iodopropynyl Butylcarbamate, Caffiene, PPG-9, Methylchloroisothiazolinone, Methylisothiazolinone

QUESTIONS

Questions, comments?: Call 1-800-761-DOVE(3683) or visit us at www.dove.com